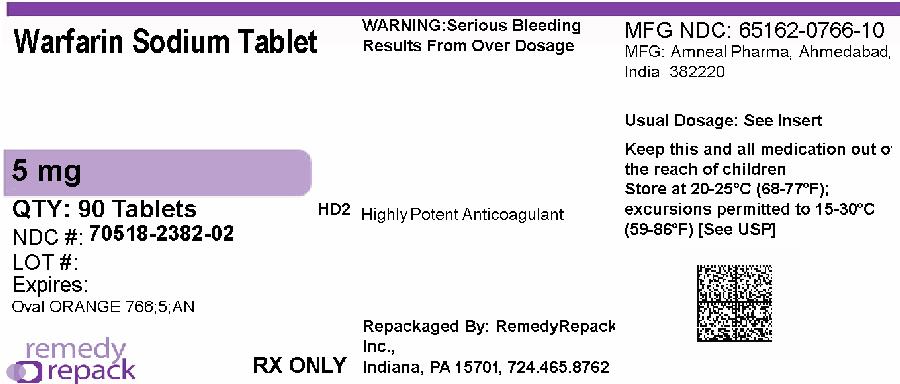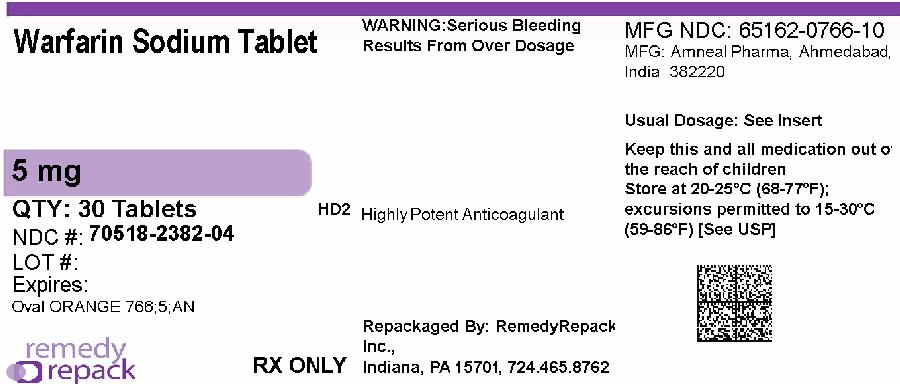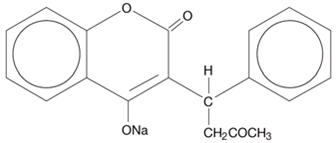 DRUG LABEL: Warfarin Sodium
NDC: 70518-2382 | Form: TABLET
Manufacturer: REMEDYREPACK INC.
Category: prescription | Type: HUMAN PRESCRIPTION DRUG LABEL
Date: 20260205

ACTIVE INGREDIENTS: WARFARIN SODIUM 5 mg/1 1
INACTIVE INGREDIENTS: HYDROXYPROPYL CELLULOSE (70000 WAMW); LACTOSE MONOHYDRATE; MAGNESIUM STEARATE; STARCH, CORN; FD&C YELLOW NO. 6

HIGHLIGHTS OF PRESCRIBING INFORMATION

These highlights do not include all the information needed to use WARFARIN SODIUM TABLETS safely and effectively. See full prescribing information for WARFARIN SODIUM TABLETS.
WARFARIN SODIUM tablets (crystalline), for oral use
Initial U.S. Approval: 1954

WARNING: BLEEDING RISK

See full prescribing information for complete boxed warning.

- Warfarin sodium can cause major or fatal bleeding. (5.1)
- Perform regular monitoring of INR in all treated patients. (2.1)
- Drugs, dietary changes, and other factors affect INR levels achieved with warfarin sodium therapy. (7)
- Instruct patients about prevention measures to minimize risk of bleeding and to report signs and symptoms of bleeding. (17)

1 INDICATIONS AND USAGE

Warfarin sodium tablets are vitamin K antagonist indicated for:

- Prophylaxis and treatment of venous thrombosis and its extension, pulmonary embolism. (1)
- Prophylaxis and treatment of thromboembolic complications associated with atrial fibrillation and/or cardiac valve replacement. (1)
- Reduction in the risk of death, recurrent myocardial infarction, and thromboembolic events such as stroke or systemic embolization after myocardial infarction. (1)

Limitations of Use

- Warfarin sodium tablets have no direct effect on an established thrombus, nor does it reverse ischemic tissue damage. (1)

2 DOSAGE AND ADMINISTRATION

- Individualize dosing regimen for each patient, and adjust based on INR response. (2.1, 2.2)
- Knowledge of genotype can inform initial dose selection. (2.3)
- Monitoring: Obtain daily INR determinations upon initiation until stable in the therapeutic range. Obtain subsequent INR determinations every 1 to 4 weeks. (2.4)
- Review conversion instructions from other anticoagulants. (2.8)

3 DOSAGE FORMS AND STRENGTHS

- Scored tablets: 5 mg (3)

4 CONTRAINDICATIONS

- Pregnancy, except in women with mechanical heart valves. (4, 5.7, 8.1)
- Hemorrhagic tendencies or blood dyscrasias. (4)
- Recent or contemplated surgery of the central nervous system (CNS) or eye, or traumatic surgery resulting in large open surfaces. (4, 5.8)
- Bleeding tendencies associated with certain conditions. (4)
- Threatened abortion, eclampsia, and preeclampsia. (4)
- Unsupervised patients with potential high levels of non-compliance. (4)
- Spinal puncture and other diagnostic or therapeutic procedures with potential for uncontrollable bleeding. (4)
- Hypersensitivity to warfarin or any component of the product. (4)
- Major regional or lumbar block anesthesia. (4)
- Malignant hypertension. (4)

5 WARNINGS AND PRECAUTIONS

- Tissue necrosis: Necrosis or gangrene of skin or other tissues can occur, with severe cases requiring debridement or amputation. Discontinue warfarin sodium and consider alternative anticoagulants if necessary. (5.2)
- Calciphylaxis: Fatal and serious cases have occurred. Discontinue warfarin sodium and consider alternative anticoagulation therapy. (5.3)
- Acute kidney injury may occur during episodes of excessive anticoagulation and hematuria. (5.4)
- Systemic atheroemboli and cholesterol microemboli: Some cases have progressed to necrosis or death. Discontinue warfarin sodium if such emboli occur. (5.5)
- Heparin-induced thrombocytopenia (HIT): Initial therapy with warfarin sodium in HIT has resulted in cases of amputation and death. Warfarin sodium may be considered after platelet count has normalized. (5.6)
- Pregnant women with mechanical heart valves: Warfarin sodium may cause fetal harm; however, the benefits may outweigh the risks. (5.7)

6 ADVERSE REACTIONS

Most common adverse reactions to warfarin sodium are fatal and nonfatal hemorrhage from any tissue or organ. (6)

To report SUSPECTED ADVERSE REACTIONS, contact Amneal Pharmaceuticals at 1-877-835-5472 or FDA at 1-800-FDA-1088 or www.fda.gov/medwatch.

7 DRUG INTERACTIONS

- Concomitant use of drugs that increase bleeding risk, antibiotics, antifungals, botanical (herbal) products, and inhibitors and inducers of CYP2C9, 1A2, or 3A4. (7)
- Consult labeling of all concurrently used drugs for complete information about interactions with warfarin sodium or increased risks for bleeding. (7)

8 USE IN SPECIFIC POPULATIONS

- Pregnant women with mechanical heart valves: warfarin sodium may cause fetal harm; however, the benefits may outweigh the risks. (8.1)
- Lactation: Monitor breastfeeding infants for bruising or bleeding. (8.2)
- Renal Impairment: Instruct patients with renal impairment to frequently monitor their INR. (8.6)

FULL PRESCRIBING INFORMATION

WARNING: BLEEDING RISK

- Warfarin sodium can cause major or fatal bleeding [see Warnings and Precautions (5.1)] .
- Perform regular monitoring of INR in all treated patients [see Dosage and Administration (2.1)] .
- Drugs, dietary changes, and other factors affect INR levels achieved with warfarin sodium therapy [see Drug Interactions (7)] .
- Instruct patients about prevention measures to minimize risk of bleeding and to report signs and symptoms of bleeding [see Patient Counseling Information (17)] .

1 INDICATIONS AND USAGE

Warfarin sodium tablets are indicated for:

- Prophylaxis and treatment of venous thrombosis and its extension, pulmonary embolism (PE).
- Prophylaxis and treatment of thromboembolic complications associated with atrial fibrillation (AF) and/or cardiac valve replacement.
- Reduction in the risk of death, recurrent myocardial infarction (MI), and thromboembolic events such as stroke or systemic embolization after myocardial infarction.

Limitations of Use

Warfarin sodium tablets have no direct effect on an established thrombus, nor does it reverse ischemic tissue damage. Once a thrombus has occurred, however, the goals of anticoagulant treatment are to prevent further extension of the formed clot and to prevent secondary thromboembolic complications that may result in serious and possibly fatal sequelae.

2 DOSAGE AND ADMINISTRATION

2.1 Individualized Dosing

The dosage and administration of warfarin sodium tablets must be individualized for each patient according to the patient’s International Normalized Ratio (INR) response to the drug. Adjust the dose based on the patient’s INR and the condition being treated. Consult the latest evidence-based clinical practice guidelines regarding the duration and intensity of anticoagulation for the indicated conditions.

2.2 Recommended Target INR Ranges and Durations for Individual Indications

An INR of greater than 4.0 appears to provide no additional therapeutic benefit in most patients and is associated with a higher risk of bleeding.

Venous Thromboembolism (including deep venous thrombosis [DVT] and PE)

Adjust the warfarin dose to maintain a target INR of 2.5 (INR range, 2.0 to 3.0) for all treatment durations. The duration of treatment is based on the indication as follows:

- For patients with a DVT or PE secondary to a transient (reversible) risk factor, treatment with warfarin for 3 months is recommended.
- For patients with an unprovoked DVT or PE, treatment with warfarin is recommended for at least 3 months. After 3 months of therapy, evaluate the risk-benefit ratio of long-term treatment for the individual patient.
- For patients with two episodes of unprovoked DVT or PE, long-term treatment with warfarin is recommended. For a patient receiving long-term anticoagulant treatment, periodically reassess the risk-benefit ratio of continuing such treatment in the individual patient.

Atrial Fibrillation

In patients with non-valvular AF, anticoagulate with warfarin to target INR of 2.5 (range, 2.0 to 3.0).

- In patients with non-valvular AF that is persistent or paroxysmal and at high risk of stroke (i.e., having any of the following features: prior ischemic stroke, transient ischemic attack, or systemic embolism, or 2 of the following risk factors: age greater than 75 years, moderately or severely impaired left ventricular systolic function and/or heart failure, history of hypertension, or diabetes mellitus), long-term anticoagulation with warfarin is recommended.
- In patients with non-valvular AF that is persistent or paroxysmal and at an intermediate risk of ischemic stroke (i.e., having 1 of the following risk factors: age greater than 75 years, moderately or severely impaired left ventricular systolic function and/or heart failure, history of hypertension, or diabetes mellitus), long-term anticoagulation with warfarin is recommended.
- For patients with AF and mitral stenosis, long-term anticoagulation with warfarin is recommended.
- For patients with AF and prosthetic heart valves, long-term anticoagulation with warfarin is recommended; the target INR may be increased and aspirin added depending on valve type and position, and on patient factors.

Mechanical and Bioprosthetic Heart Valves

- For patients with a bileaflet mechanical valve or a Medtronic Hall (Minneapolis, MN) tilting disk valve in the aortic position who are in sinus rhythm and without left atrial enlargement, therapy with warfarin to a target INR of 2.5 (range, 2.0 to 3.0) is recommended.
- For patients with tilting disk valves and bileaflet mechanical valves in the mitral position, therapy with warfarin to a target INR of 3.0 (range, 2.5 to 3.5) is recommended.
- For patients with caged ball or caged disk valves, therapy with warfarin to a target INR of 3.0 (range, 2.5 to 3.5) is recommended.
- For patients with a bioprosthetic valve in the mitral position, therapy with warfarin to a target INR of 2.5 (range, 2.0 to 3.0) for the first 3 months after valve insertion is recommended. If additional risk factors for thromboembolism are present (AF, previous thromboembolism, left ventricular dysfunction), a target INR of 2.5 (range, 2.0 to 3.0) is recommended.

Post-Myocardial Infarction

- For high-risk patients with MI (e.g., those with a large anterior MI, those with significant heart failure, those with intracardiac thrombus visible on transthoracic echocardiography, those with AF, and those with a history of a thromboembolic event), therapy with combined moderate-intensity (INR, 2.0 to 3.0) warfarin plus low-dose aspirin (≤100 mg/day) for at least 3 months after the MI is recommended.

Recurrent Systemic Embolism and Other Indications

Oral anticoagulation therapy with warfarin has not been fully evaluated by clinical trials in patients with valvular disease associated with AF, patients with mitral stenosis, and patients with recurrent systemic embolism of unknown etiology. However, a moderate dose regimen (INR 2.0 to 3.0) may be used for these patients.

2.3 Initial and Maintenance Dosing

The appropriate initial dosing of warfarin sodium tablets varies widely for different patients. Not all factors responsible for warfarin dose variability are known, and the initial dose is influenced by:

- Clinical factors including age, race, body weight, sex, concomitant medications, and comorbidities
- Genetic factors (CYP2C9 and VKORC1 genotypes) [see Clinical Pharmacology (12.5)]

Select the initial dose based on the expected maintenance dose, taking into account the above factors. Modify this dose based on consideration of patient-specific clinical factors. Consider lower initial and maintenance doses for elderly and/or debilitated patients and in Asian patients [see Use in Specific Populations (8.5) and Clinical Pharmacology (12.3)] . Routine use of loading doses is not recommended as this practice may increase hemorrhagic and other complications and does not offer more rapid protection against clot formation.

Individualize the duration of therapy for each patient. In general, anticoagulant therapy should be continued until the danger of thrombosis and embolism has passed [ see Dosage and Administration (2.2)] .

Dosing Recommendations without Consideration of Genotype

If the patient’s CYP2C9 and VKORC1 genotypes are not known, the initial dose of warfarin sodium tablets is usually 2 mg to 5 mg once daily. Determine each patient’s dosing needs by close monitoring of the INR response and consideration of the indication being treated. Typical maintenance doses are 2 mg to 10 mg once daily.

Dosing Recommendations with Consideration of Genotype

Table 1 displays three ranges of expected maintenance warfarin sodium tablets doses observed in subgroups of patients having different combinations of CYP2C9 and VKORC1 gene variants [see Clinical Pharmacology (12.5)] . If the patient’s CYP2C9 and/or VKORC1 genotype are known, consider these ranges in choosing the initial dose. Patients with CYP2C9 *1/*3, *2/*2, *2/*3, and *3/*3 may require more prolonged time (>2 to 4 weeks) to achieve maximum INR effect for a given dosage regimen than patients without these CYP variants.

Table 1: Three Ranges of Expected Maintenance Warfarin Sodium Tablets Daily Doses Based on CYP2C9 and VKORC1 Genotypes†
VKORC1 | CYP2C9
 | *1/*1 | *1/*2 | *1/*3 | *2/*2 | *2/*3 | *3/*3
GG | 5 mg to 7 mg | 5 mg to 7 mg | 3 mg to 4 mg | 3 mg to 4 mg | 3 mg to 4 mg | 0.5 mg to 2 mg
AG | 5 mg to 7 mg | 3 mg to 4 mg | 3 mg to 4 mg | 3 mg to 4 mg | 0.5 mg to 2 mg | 0.5 mg to 2 mg
AA | 3 mg to 4 mg | 3 mg to 4 mg | 0.5 mg to 2 mg | 0.5 mg to 2 mg | 0.5 mg to 2 mg | 0.5 mg to 2 mg
†Ranges are derived from multiple published clinical studies. VKORC1 -1639G>A (rs9923231) variant is used in this table. Other co-inherited VKORC1 variants may also be important determinants of warfarin dose.

2.4 Monitoring to Achieve Optimal Anticoagulation

Warfarin sodium tablets have a narrow therapeutic range (index), and its action may be affected by factors such as other drugs and dietary vitamin K. Therefore, anticoagulation must be carefully monitored during warfarin sodium tablets therapy. Determine the INR daily after the administration of the initial dose until INR results stabilize in the therapeutic range. After stabilization, maintain dosing within the therapeutic range by performing periodic INRs. The frequency of performing INR should be based on the clinical situation but generally acceptable intervals for INR determinations are 1 to 4 weeks. Perform additional INR tests when other warfarin products are interchanged with warfarin sodium tablets as well as whenever other medications are initiated, discontinued, or taken irregularly. Heparin, a common concomitant drug, increases the INR [see Dosage and Administration (2.8) and Drug Interactions (7)] .

Determinations of whole blood clotting and bleeding times are not effective measures for monitoring of warfarin sodium tablets therapy.

2.5 Renal Impairment

No dosage adjustment is necessary for patients with renal failure. Monitor INR more frequently in patients with compromised renal function to maintain INR within the therapeutic range [see Warnings and Precautions (5.4) and Use in Specific Populations (8.6)].

2.6 Missed Dose

The anticoagulant effect of warfarin sodium tablets persists beyond 24 hours. If a patient misses a dose of warfarin sodium tablets at the intended time of day, the patient should take the dose as soon as possible on the same day. The patient should not double the dose the next day to make up for a missed dose.

2.7 Treatment During Dentistry and Surgery

Some dental or surgical procedures may necessitate the interruption or change in the dose of warfarin sodium tablets therapy. Consider the benefits and risks when discontinuing warfarin sodium tablets even for a short period of time. Determine the INR immediately prior to any dental or surgical procedure. In patients undergoing minimally invasive procedures who must be anticoagulated prior to, during, or immediately following these procedures, adjusting the dosage of warfarin sodium tablets to maintain the INR at the low end of the therapeutic range may safely allow for continued anticoagulation.

2.8 Conversion From Other Anticoagulants

Heparin

Since the full anticoagulant effect of warfarin sodium tablets is not achieved for several days, heparin is preferred for initial rapid anticoagulation. During initial therapy with warfarin sodium tablets, the interference with heparin anticoagulation is of minimal clinical significance. Conversion to warfarin sodium tablets may begin concomitantly with heparin therapy or may be delayed 3 to 6 days. To ensure therapeutic anticoagulation, continue full dose heparin therapy and overlap warfarin sodium tablets therapy with heparin for 4 to 5 days and until warfarin sodium tablets has produced the desired therapeutic response as determined by INR, at which point heparin may be discontinued.

As heparin may affect the INR, patients receiving both heparin and warfarin sodium tablets should have INR monitoring at least:

- 5 hours after the last intravenous bolus dose of heparin, or
- 4 hours after cessation of a continuous intravenous infusion of heparin, or
- 24 hours after the last subcutaneous heparin injection.

Warfarin sodium tablets may increase the activated partial thromboplastin time (aPTT) test, even in the absence of heparin. A severe elevation (>50 seconds) in aPTT with an INR in the desired range has been identified as an indication of increased risk of postoperative hemorrhage.

Other Anticoagulants

Consult the labeling of other anticoagulants for instructions on conversion to warfarin sodium tablets.

3 DOSAGE FORMS AND STRENGTHS

Warfarin Sodium Tablets USP, 5 mg are supplied as peach to light peach, oval shaped uncoated scored tablets with debossing ‘766’ and ‘5’ on either side of the breakline on one side and ‘AN’ on the other side.

4 CONTRAINDICATIONS

Warfarin sodium is contraindicated in:

- Pregnancy

Warfarin sodium is contraindicated in women who are pregnant except in pregnant women with mechanical heart valves, who are at high risk of thromboembolism [see Warnings and Precautions (5.7) and Use in Specific Populations (8.1)] . Warfarin sodium can cause fetal harm when administered to a pregnant woman. Warfarin sodium exposure during pregnancy causes a recognized pattern of major congenital malformations (warfarin embryopathy and fetotoxicity), fatal fetal hemorrhage, and an increased risk of spontaneous abortion and fetal mortality. If warfarin sodium is used during pregnancy or if the patient becomes pregnant while taking this drug, the patient should be apprised of the potential hazard to a fetus [see Use in Specific Populations (8.1)] .

Warfarin sodium is contraindicated in patients with:

- Hemorrhagic tendencies or blood dyscrasias
- Recent or contemplated surgery of the central nervous system or eye, or traumatic surgery resulting in large open surfaces [see Warnings and Precautions (5.8)]
- Bleeding tendencies associated with:
  − Active ulceration or overt bleeding of the gastrointestinal, genitourinary, or respiratory tract
  − Central nervous system hemorrhage
  − Cerebral aneurysms, dissecting aorta
  − Pericarditis and pericardial effusions
  − Bacterial endocarditis
- Threatened abortion, eclampsia, and preeclampsia
- Unsupervised patients with conditions associated with potential high level of non-compliance
- Spinal puncture and other diagnostic or therapeutic procedures with potential for uncontrollable bleeding
- Hypersensitivity to warfarin or to any other components of this product (e.g., anaphylaxis) [see Adverse Reactions (6)]
- Major regional or lumbar block anesthesia
- Malignant hypertension

5 WARNINGS AND PRECAUTIONS

5.1 Hemorrhage

Warfarin sodium can cause major or fatal bleeding. Bleeding is more likely to occur within the first month. Risk factors for bleeding include high intensity of anticoagulation (INR >4.0), age greater than or equal to 65, history of highly variable INRs, history of gastrointestinal bleeding, hypertension, cerebrovascular disease, anemia, malignancy, trauma, renal impairment, certain genetic factors [see Clinical Pharmacology (12.5)] , certain concomitant drugs [see Drug Interactions (7)] , and long duration of warfarin therapy.

Perform regular monitoring of INR in all treated patients. Those at high risk of bleeding may benefit from more frequent INR monitoring, careful dose adjustment to desired INR, and a shortest duration of therapy appropriate for the clinical condition. However, maintenance of INR in the therapeutic range does not eliminate the risk of bleeding.

Drugs, dietary changes, and other factors affect INR levels achieved with warfarin sodium therapy. Perform more frequent INR monitoring when starting or stopping other drugs, including botanicals, or when changing dosages of other drugs [see Drug Interactions (7)] .

Instruct patients about prevention measures to minimize risk of bleeding and to report signs and symptoms of bleeding [see Patient Counseling Information (17)] .

5.2 Tissue Necrosis

Warfarin sodium can cause necrosis and/or gangrene of skin and other tissues, which is an uncommon but serious risk (<0.1%). Necrosis may be associated with local thrombosis and usually appears within a few days of the start of warfarin sodium therapy. In severe cases of necrosis, treatment through debridement or amputation of the affected tissue, limb, breast, or penis has been reported.

Careful clinical evaluation is required to determine whether necrosis is caused by an underlying disease. Although various treatments have been attempted, no treatment for necrosis has been considered uniformly effective. Discontinue warfarin sodium therapy if necrosis occurs. Consider alternative drugs if continued anticoagulation therapy is necessary.

5.3 Calciphylaxis

Warfarin sodium can cause fatal and serious calciphylaxis or calcium uremic arteriolopathy, which has been reported in patients with and without end-stage renal disease. When calciphylaxis is diagnosed in these patients, discontinue warfarin sodium and treat calciphylaxis as appropriate. Consider alternative anticoagulation therapy.

5.4 Acute Kidney Injury

In patients with altered glomerular integrity or with a history of kidney disease, acute kidney injury may occur with warfarin sodium, possibly in relation to episodes of excessive anticoagulation and hematuria [see Use in Specific Populations (8.6)] . More frequent monitoring of anticoagulation is advised in patients with compromised renal function.

5.5 Systemic Atheroemboli and Cholesterol Microemboli

Anticoagulation therapy with warfarin sodium may enhance the release of atheromatous plaque emboli. Systemic atheroemboli and cholesterol microemboli can present with a variety of signs and symptoms depending on the site of embolization. The most commonly involved visceral organs are the kidneys followed by the pancreas, spleen, and liver. Some cases have progressed to necrosis or death. A distinct syndrome resulting from microemboli to the feet is known as “purple toes syndrome.” Discontinue warfarin sodium therapy if such phenomena are observed. Consider alternative drugs if continued anticoagulation therapy is necessary.

5.6 Limb Ischemia, Necrosis, and Gangrene in Patients with HIT and HITTS

Do not use warfarin sodium as initial therapy in patients with heparin-induced thrombocytopenia (HIT) and with heparin-induced thrombocytopenia with thrombosis syndrome (HITTS). Cases of limb ischemia, necrosis, and gangrene have occurred in patients with HIT and HITTS when heparin treatment was discontinued and warfarin therapy was started or continued. In some patients, sequelae have included amputation of the involved area and/or death. Treatment with warfarin sodium may be considered after the platelet count has normalized.

5.7 Use in Pregnant Women with Mechanical Heart Valves

Warfarin sodium can cause fetal harm when administered to a pregnant woman. While warfarin sodium is contraindicated during pregnancy, the potential benefits of using warfarin sodium may outweigh the risks for pregnant women with mechanical heart valves at high risk of thromboembolism. In those individual situations, the decision to initiate or continue warfarin sodium should be reviewed with the patient, taking into consideration the specific risks and benefits pertaining to the individual patient’s medical situation, as well as the most current medical guidelines. Warfarin sodium exposure during pregnancy causes a recognized pattern of major congenital malformations (warfarin embryopathy and fetotoxicity), fatal fetal hemorrhage, and an increased risk of spontaneous abortion and fetal mortality. If this drug is used during pregnancy, or if the patient becomes pregnant while taking this drug, the patient should be apprised of the potential hazard to a fetus [see Use in Specific Populations (8.1)] .

5.8 Other Clinical Settings with Increased Risks

In the following clinical settings, the risks of warfarin sodium therapy may be increased:

- Moderate to severe hepatic impairment
- Infectious diseases or disturbances of intestinal flora (e.g., sprue, antibiotic therapy)
- Use of an indwelling catheter
- Severe to moderate hypertension
- Deficiency in protein C-mediated anticoagulant response: warfarin sodium reduces the synthesis of the naturally occurring anticoagulants, protein C and protein S. Hereditary or acquired deficiencies of protein C or its cofactor, protein S, have been associated with tissue necrosis following warfarin administration. Concomitant anticoagulation therapy with heparin for 5 to 7 days during initiation of therapy with warfarin sodium may minimize the incidence of tissue necrosis in these patients.
- Eye surgery: In cataract surgery, warfarin sodium use was associated with a significant increase in minor complications of sharp needle and local anesthesia block but not associated with potentially sight-threatening operative hemorrhagic complications. As warfarin sodium cessation or reduction may lead to serious thromboembolic complications, the decision to discontinue warfarin sodium before a relatively less invasive and complex eye surgery, such as lens surgery, should be based upon the risks of anticoagulant therapy weighed against the benefits.
- Polycythemia vera
- Vasculitis
- Diabetes mellitus

5.9 Endogenous Factors Affecting INR

The following factors may be responsible for increased INR response: diarrhea, hepatic disorders, poor nutritional state, steatorrhea, or vitamin K deficiency.

The following factors may be responsible for decreased INR response: increased vitamin K intake or hereditary warfarin resistance.

6 ADVERSE REACTIONS

The following serious adverse reactions to warfarin sodium are discussed in greater detail in other sections of the labeling:

- Hemorrhage [see Boxed Warning, Warnings and Precautions (5.1), and Overdosage (10)]
- Tissue Necrosis [see Warnings and Precautions (5.2)]
- Calciphylaxis [see Warnings and Precautions (5.3)]
- Acute Kidney Injury [see Warnings and Precautions (5.4)]
- Systemic Atheroemboli and Cholesterol Microemboli [see Warnings and Precautions (5.5)]
- Limb Ischemia, Necrosis, and Gangrene in Patients with HIT and HITTS [see Warnings and Precautions (5.6)]
- Other Clinical Settings with Increased Risks [see Warnings and Precautions (5.8)]

Other adverse reactions to warfarin sodium include:

- Immune system disorders: hypersensitivity/allergic reactions (including urticaria and anaphylactic reactions)
- Vascular disorders: vasculitis
- Hepatobiliary disorders: hepatitis, elevated liver enzymes. Cholestatic hepatitis has been associated with concomitant administration of warfarin sodium and ticlopidine.
- Gastrointestinal disorders: nausea, vomiting, diarrhea, taste perversion, abdominal pain, flatulence, bloating
- Skin disorders: rash, dermatitis (including bullous eruptions), pruritus, alopecia
- Respiratory disorders: tracheal or tracheobronchial calcification
- General disorders: chills

7 DRUG INTERACTIONS

7.1 General Information

Drugs may interact with warfarin sodium through pharmacodynamic or pharmacokinetic mechanisms. Pharmacodynamic mechanisms for drug interactions with warfarin sodium are synergism (impaired hemostasis, reduced clotting factor synthesis), competitive antagonism (vitamin K), and alteration of the physiologic control loop for vitamin K metabolism (hereditary resistance). Pharmacokinetic mechanisms for drug interactions with warfarin sodium are mainly enzyme induction, enzyme inhibition, and reduced plasma protein binding. It is important to note that some drugs may interact by more than one mechanism.

More frequent INR monitoring should be performed when starting or stopping other drugs, including botanicals, or when changing dosages of other drugs, including drugs intended for short-term use (e.g., antibiotics, antifungals, corticosteroids) [see Boxed Warning] .

Consult the labeling of all concurrently used drugs to obtain further information about interactions with warfarin sodium or adverse reactions pertaining to bleeding.

7.2 CYP450 Interactions

CYP450 isozymes involved in the metabolism of warfarin include CYP2C9, 2C19, 2C8, 2C18, 1A2, and 3A4. The more potent warfarin S-enantiomer is metabolized by CYP2C9 while the R-enantiomer is metabolized by CYP1A2 and 3A4.

- Inhibitors of CYP2C9, 1A2, and/or 3A4 have the potential to increase the effect (increase INR) of warfarin by increasing the exposure of warfarin.
- Inducers of CYP2C9, 1A2, and/or 3A4 have the potential to decrease the effect (decrease INR) of warfarin by decreasing the exposure of warfarin.

Examples of inhibitors and inducers of CYP2C9, 1A2, and 3A4 are below in Table 2; however, this list should not be considered all-inclusive. Consult the labeling of all concurrently used drugs to obtain further information about CYP450 interaction potential. The CYP450 inhibition and induction potential should be considered when starting, stopping, or changing dose of concomitant medications. Closely monitor INR if a concomitant drug is a CYP2C9, 1A2, and/or 3A4 inhibitor or inducer.

Table 2: Examples of CYP450 Interactions with Warfarin
Enzyme | Inhibitors | Inducers
CYP2C9 | amiodarone, capecitabine, cotrimoxazole, etravirine, fluconazole, fluvastatin, fluvoxamine, metronidazole, miconazole, oxandrolone, sulfinpyrazone, tigecycline, voriconazole, zafirlukast | aprepitant, bosentan, carbamazepine, phenobarbital, rifampin
CYP1A2 | acyclovir, allopurinol, caffeine, cimetidine, ciprofloxacin, disulfiram, enoxacin, famotidine, fluvoxamine, methoxsalen, mexiletine, norfloxacin, oral contraceptives, phenylpropanolamine, propafenone, propranolol, terbinafine, thiabendazole, ticlopidine, verapamil, zileuton | montelukast, moricizine, omeprazole, phenobarbital, phenytoin, cigarette smoking
CYP3A4 | alprazolam, amiodarone, amlodipine, amprenavir, aprepitant, atorvastatin, atazanavir, bicalutamide, cilostazol, cimetidine, ciprofloxacin, clarithromycin, conivaptan, cyclosporine, darunavir/ritonavir, diltiazem, erythromycin, fluconazole, fluoxetine, fluvoxamine, fosamprenavir, imatinib, indinavir, isoniazid, itraconazole, ketoconazole, lopinavir/ritonavir, nefazodone, nelfinavir, nilotinib, oral contraceptives, posaconazole, ranitidine, ranolazine, ritonavir, saquinavir, telithromycin, tipranavir, voriconazole, zileuton | armodafinil, amprenavir, aprepitant, bosentan, carbamazepine, efavirenz, etravirine, modafinil, nafcillin, phenytoin, pioglitazone, prednisone, rifampin, rufinamide

7.3 Drugs that Increase Bleeding Risk

Examples of drugs known to increase the risk of bleeding are presented in Table 3. Because bleeding risk is increased when these drugs are used concomitantly with warfarin, closely monitor patients receiving any such drug with warfarin.

Table 3: Drugs that Can Increase the Risk of Bleeding
Drug Class | Specific Drugs
Anticoagulants | argatroban, dabigatran, bivalirudin, desirudin, heparin, lepirudin
Antiplatelet Agents | aspirin, cilostazol, clopidogrel, dipyridamole, prasugrel, ticlopidine
Nonsteroidal Anti-Inflammatory Agents | celecoxib, diclofenac, diflunisal, fenoprofen, ibuprofen, indomethacin, ketoprofen, ketorolac, mefenamic acid, naproxen, oxaprozin, piroxicam, sulindac
Serotonin Reuptake Inhibitors | citalopram, desvenlafaxine, duloxetine, escitalopram, fluoxetine, fluvoxamine, milnacipran, paroxetine, sertraline, venlafaxine, vilazodone

7.4 Antibiotics and Antifungals

There have been reports of changes in INR in patients taking warfarin and antibiotics or antifungals, but clinical pharmacokinetic studies have not shown consistent effects of these agents on plasma concentrations of warfarin.

Closely monitor INR when starting or stopping any antibiotic or antifungal in patients taking warfarin.

7.5 Botanical (Herbal) Products and Foods

More frequent INR monitoring should be performed when starting or stopping botanicals.

Few adequate, well-controlled studies evaluating the potential for metabolic and/or pharmacologic interactions between botanicals and warfarin sodium exist. Due to a lack of manufacturing standardization with botanical medicinal preparations, the amount of active ingredients may vary. This could further confound the ability to assess potential interactions and effects on anticoagulation.

Some botanicals may cause bleeding events when taken alone (e.g., garlic and Ginkgo biloba) and may have anticoagulant, antiplatelet, and/or fibrinolytic properties. These effects would be expected to be additive to the anticoagulant effects of warfarin sodium. Conversely, some botanicals may decrease the effects of warfarin sodium (e.g., co-enzyme Q10, St. John’s wort, ginseng). Some botanicals and foods can interact with warfarin sodium through CYP450 interactions (e.g., echinacea, grapefruit juice, ginkgo, goldenseal, St. John’s wort).

The amount of vitamin K in food may affect therapy with warfarin sodium. Advise patients taking warfarin sodium to eat a normal, balanced diet maintaining a consistent amount of vitamin K. Patients taking warfarin sodium should avoid drastic changes in dietary habits, such as eating large amounts of green leafy vegetables.

8 USE IN SPECIFIC POPULATIONS

8.1 Pregnancy

Risk Summary

Warfarin sodium is contraindicated in women who are pregnant except in pregnant women with mechanical heart valves, who are at high risk of thromboembolism, and for whom the benefits of warfarin sodium may outweigh the risks [see Warnings and Precautions (5.7)] . Warfarin sodium can cause fetal harm. Exposure to warfarin during the first trimester of pregnancy caused a pattern of congenital malformations in about 5% of exposed offspring. Because these data were not collected in adequate and well-controlled studies, this incidence of major birth defects is not an adequate basis for comparison to the estimated incidences in the control group or the U.S. general population and may not reflect the incidences observed in practice. Consider the benefits and risks of warfarin sodium and possible risks to the fetus when prescribing warfarin sodium to a pregnant woman.

Adverse outcomes in pregnancy occur regardless of the health of the mother or the use of medications. The estimated background risk of major birth defects and miscarriage for the indicated population is unknown. In the U.S. general population, the estimated background risk of major birth defects and miscarriage in clinically recognized pregnancies is 2% to 4% and 15% to 20%, respectively.

Clinical Considerations

Fetal/Neonatal Adverse Reactions

In humans, warfarin crosses the placenta, and concentrations in fetal plasma approach the maternal values. Exposure to warfarin during the first trimester of pregnancy caused a pattern of congenital malformations in about 5% of exposed offspring. Warfarin embryopathy is characterized by nasal hypoplasia with or without stippled epiphyses (chondrodysplasia punctata) and growth retardation (including low birth weight). Central nervous system and eye abnormalities have also been reported, including dorsal midline dysplasia characterized by agenesis of the corpus callosum, Dandy-Walker malformation, midline cerebellar atrophy, and ventral midline dysplasia characterized by optic atrophy. Mental retardation, blindness, schizencephaly, microcephaly, hydrocephalus, and other adverse pregnancy outcomes have been reported following warfarin exposure during the second and third trimesters of pregnancy [see Contraindications (4)].

8.2 Lactation

Risk Summary

Warfarin was not present in human milk from mothers treated with warfarin from a limited published study. Because of the potential for serious adverse reactions, including bleeding in a breastfed infant, consider the developmental and health benefits of breastfeeding along with the mother’s clinical need for warfarin sodium and any potential adverse effects on the breastfed infant from warfarin sodium or from the underlying maternal condition before prescribing warfarin sodium to a lactating woman.

Clinical Considerations

Monitor breastfeeding infants for bruising or bleeding.

Data

Human Data

Based on published data in 15 nursing mothers, warfarin was not detected in human milk. Among the 15 full-term newborns, 6 nursing infants had documented prothrombin times within the expected range. Prothrombin times were not obtained for the other 9 nursing infants. Effects in premature infants have not been evaluated.

8.3 Females and Males of Reproductive Potential

Pregnancy Testing

Warfarin sodium can cause fetal harm [see Use in Specific Populations (8.1)].

Verify the pregnancy status of females of reproductive potential prior to initiating warfarin sodium therapy.

Contraception

Females

Advise females of reproductive potential to use effective contraception during treatment and for at least 1 month after the final dose of warfarin sodium.

8.4 Pediatric Use

Adequate and well-controlled studies with warfarin sodium have not been conducted in any pediatric population, and the optimum dosing, safety, and efficacy in pediatric patients is unknown. Pediatric use of warfarin sodium is based on adult data and recommendations, and available limited pediatric data from observational studies and patient registries. Pediatric patients administered warfarin sodium should avoid any activity or sport that may result in traumatic injury.

The developing hemostatic system in infants and children results in a changing physiology of thrombosis and response to anticoagulants. Dosing of warfarin in the pediatric population varies by patient age, with infants generally having the highest, and adolescents having the lowest milligram per kilogram dose requirements to maintain target INRs. Because of changing warfarin requirements due to age, concomitant medications, diet, and existing medical condition, target INR ranges may be difficult to achieve and maintain in pediatric patients, and more frequent INR determinations are recommended. Bleeding rates varied by patient population and clinical care center in pediatric observational studies and patient registries.

Infants and children receiving vitamin K-supplemented nutrition, including infant formulas, may be resistant to warfarin therapy, while human milk-fed infants may be sensitive to warfarin therapy.

8.5 Geriatric Use

Of the total number of patients receiving warfarin sodium in controlled clinical trials for which data were available for analysis, 1885 patients (24.4%) were 65 years and older, while 185 patients (2.4%) were 75 years and older. No overall differences in effectiveness or safety were observed between these patients and younger patients, but greater sensitivity of some older individuals cannot be ruled out.

Patients 60 years or older appear to exhibit greater than expected INR response to the anticoagulant effects of warfarin [see Clinical Pharmacology (12.3)] . Warfarin sodium is contraindicated in any unsupervised patient with senility. Conduct more frequent monitoring for bleeding with administration of warfarin sodium to elderly patients in any situation or with any physical condition where added risk of hemorrhage is present. Consider lower initiation and maintenance doses of warfarin sodium in elderly patients [see Dosage and Administration (2.2, 2.3)] .

8.6 Renal Impairment

Renal clearance is considered to be a minor determinant of anticoagulant response to warfarin. No dosage adjustment is necessary for patients with renal impairment. Instruct patients with renal impairment taking warfarin to monitor their INR more frequently [see Warnings and Precautions (5.4)] .

8.7 Hepatic Impairment

Hepatic impairment can potentiate the response to warfarin through impaired synthesis of clotting factors and decreased metabolism of warfarin. Conduct more frequent monitoring for bleeding when using warfarin sodium in these patients.

10 OVERDOSAGE

10.1 Signs and Symptoms

Bleeding (e.g., appearance of blood in stools or urine, hematuria, excessive menstrual bleeding, melena, petechiae, excessive bruising or persistent oozing from superficial injuries, unexplained fall in hemoglobin) is a manifestation of excessive anticoagulation.

10.2 Treatment

The treatment of excessive anticoagulation is based on the level of the INR, the presence or absence of bleeding, and clinical circumstances. Reversal of warfarin sodium anticoagulation may be obtained by discontinuing warfarin sodium therapy and, if necessary, by administration of oral or parenteral vitamin K1.

The use of vitamin K1 reduces response to subsequent warfarin sodium therapy and patients may return to a pretreatment thrombotic status following the rapid reversal of a prolonged INR. Resumption of warfarin sodium administration reverses the effect of vitamin K, and a therapeutic INR can again be obtained by careful dosage adjustment. If rapid re-anticoagulation is indicated, heparin may be preferable for initial therapy.

Prothrombin complex concentrate (PCC), fresh frozen plasma, or activated Factor VII treatment may be considered if the requirement to reverse the effects of warfarin sodium is urgent. A risk of hepatitis and other viral diseases is associated with the use of blood products; PCC and activated Factor VII are also associated with an increased risk of thrombosis. Therefore, these preparations should be used only in exceptional or life-threatening bleeding episodes secondary to warfarin sodium overdosage.

11 DESCRIPTION

Crystalline warfarin sodium is an anticoagulant that acts by inhibiting vitamin K-dependent coagulation factors. The chemical name of warfarin sodium is 3-(α-acetonylbenzyl)-4-hydroxycoumarin sodium salt, which is a racemic mixture of the R- and S-enantiomers. Crystalline warfarin sodium is an isopropanol clathrate. Its empirical formula is C19H15NaO4, and its structural formula is represented by the following:

Crystalline warfarin sodium occurs as a white, odorless, crystalline powder that is discolored by light. It is very soluble in water, freely soluble in alcohol, and very slightly soluble in chloroform and ether.

Warfarin sodium tablets, USP (Crystalline) for oral use also contain:

All strengths: Hydroxypropyl Cellulose, Lactose Monohydrate, Magnesium Stearate and Pregelatinized Starch

1 mg: D&C Red No. 6 Barium Lake

2 mg: FD&C Blue No. 2 Aluminum Lake and FD&C Red No. 40 Aluminum Lake

2-1/2 mg: D&C Yellow No. 10 Aluminum Lake and FD&C Blue No. 1 Aluminum Lake

3 mg: FD&C Yellow No. 6 Aluminum Lake, FD&C Blue No. 2 Aluminum Lake, and FD&C Red No. 40 Aluminum Lake

4 mg: FD&C Blue No. 1 Aluminum Lake

5 mg: FD&C Yellow No. 6 Aluminum Lake

6 mg: FD&C Yellow No. 6 Aluminum Lake and FD&C Blue No. 1 Aluminum Lake

7-1/2 mg: D&C Yellow No. 10 Aluminum Lake and FD&C Yellow No. 6 Aluminum Lake

10 mg: Dye-free

12 CLINICAL PHARMACOLOGY

12.1 Mechanism of Action

Warfarin acts by inhibiting the synthesis of vitamin K-dependent clotting factors, which include Factors II, VII, IX, and X, and the anticoagulant proteins C and S. Vitamin K is an essential cofactor for the post ribosomal synthesis of the vitamin K-dependent clotting factors. Vitamin K promotes the biosynthesis of γ-carboxyglutamic acid residues in the proteins that are essential for biological activity. Warfarin is thought to interfere with clotting factor synthesis by inhibition of the C1 subunit of vitamin K epoxide reductase (VKORC1) enzyme complex, thereby reducing the regeneration of vitamin K1 epoxide [see Clinical Pharmacology (12.5)] .

12.2 Pharmacodynamics

An anticoagulation effect generally occurs within 24 hours after warfarin administration. However, peak anticoagulant effect may be delayed 72 to 96 hours. The duration of action of a single dose of racemic warfarin is 2 to 5 days. The effects of warfarin sodium may become more pronounced as effects of daily maintenance doses overlap. This is consistent with the half-lives of the affected vitamin K-dependent clotting factors and anticoagulation proteins: Factor II - 60 hours, VII - 4 to 6 hours, IX - 24 hours, X - 48 to 72 hours, and proteins C and S are approximately 8 hours and 30 hours, respectively.

12.3 Pharmacokinetics

Warfarin sodium is a racemic mixture of the R- and S-enantiomers of warfarin. The S-enantiomer exhibits 2 to 5 times more anticoagulant activity than the R-enantiomer in humans, but generally has a more rapid clearance.

Absorption

Warfarin is essentially completely absorbed after oral administration, with peak concentration generally attained within the first 4 hours.

Distribution

Warfarin shows a volume of distribution of about 0.14 L/kg. Approximately 99% of the drug is bound to plasma proteins.

Metabolism

The elimination of warfarin is almost entirely by metabolism. Warfarin is stereoselectively metabolized by hepatic cytochrome P-450 (CYP450) microsomal enzymes to inactive hydroxylated metabolites (predominant route) and by reductases to reduced metabolites (warfarin alcohols) with minimal anticoagulant activity. Identified metabolites of warfarin include dehydrowarfarin, two diastereoisomer alcohols, and 4′-, 6-, 7-, 8-, and 10- hydroxywarfarin. The CYP450 isozymes involved in the metabolism of warfarin include CYP2C9, 2C19, 2C8, 2C18, 1A2, and 3A4. CYP2C9, a polymorphic enzyme, is likely to be the principal form of human liver CYP450 that modulates the in vivo anticoagulant activity of warfarin. Patients with one or more variant CYP2C9 alleles have decreased S-warfarin clearance [see Clinical Pharmacology (12.5)] .

Excretion

The terminal half-life of warfarin after a single dose is approximately 1 week; however, the effective half-life ranges from 20 to 60 hours, with a mean of about 40 hours. The clearance of R-warfarin is generally half that of S-warfarin, thus as the volumes of distribution are similar, the half-life of R-warfarin is longer than that of S-warfarin. The half-life of R-warfarin ranges from 37 to 89 hours, while that of S-warfarin ranges from 21 to 43 hours. Studies with radiolabeled drug have demonstrated that up to 92% of the orally administered dose is recovered in urine. Very little warfarin is excreted unchanged in urine. Urinary excretion is in the form of metabolites.

Geriatric Patients

Patients 60 years or older appear to exhibit greater than expected INR response to the anticoagulant effects of warfarin. The cause of the increased sensitivity to the anticoagulant effects of warfarin in this age group is unknown but may be due to a combination of pharmacokinetic and pharmacodynamic factors. Limited information suggests there is no difference in the clearance of S-warfarin; however, there may be a slight decrease in the clearance of R-warfarin in the elderly as compared to the young. Therefore, as patient age increases, a lower dose of warfarin is usually required to produce a therapeutic level of anticoagulation [see Dosage and Administration (2.3, 2.4)] .

Asian Patients

Asian patients may require lower initiation and maintenance doses of warfarin. A non-controlled study of 151 Chinese outpatients stabilized on warfarin for various indications reported a mean daily warfarin requirement of 3.3 ± 1.4 mg to achieve an INR of 2 to 2.5. Patient age was the most important determinant of warfarin requirement in these patients, with a progressively lower warfarin requirement with increasing age.

12.5 Pharmacogenomics

CYP2C9 and VKORC1 Polymorphisms

The S-enantiomer of warfarin is mainly metabolized to 7-hydroxywarfarin by CYP2C9, a polymorphic enzyme. The variant alleles, CYP2C9*2 and CYP2C9*3, result in decreased in vitro CYP2C9 enzymatic 7-hydroxylation of S-warfarin. The frequencies of these alleles in Caucasians are approximately 11% and 7% for CYP2C9*2 and CYP2C9*3, respectively.

Other CYP2C9 alleles associated with reduced enzymatic activity occur at lower frequencies, including *5, *6, and *11 alleles in populations of African ancestry and *5, *9, and *11 alleles in Caucasians.

Warfarin reduces the regeneration of vitamin K from vitamin K epoxide in the vitamin K cycle through inhibition of VKOR, a multiprotein enzyme complex. Certain single nucleotide polymorphisms in the VKORC1 gene (e.g., –1639G>A) have been associated with variable warfarin dose requirements. VKORC1 and CYP2C9 gene variants generally explain the largest proportion of known variability in warfarin dose requirements.

CYP2C9 and VKORC1 genotype information, when available, can assist in selection of the initial dose of warfarin [see Dosage and Administration (2.3)] .

13 NONCLINICAL TOXICOLOGY

13.1 Carcinogenesis, Mutagenesis, Impairment of Fertility

Carcinogenicity, mutagenicity, or fertility studies have not been performed with warfarin.

14 CLINICAL STUDIES

14.1 Atrial Fibrillation

In five prospective, randomized, controlled clinical trials involving 3711 patients with non-rheumatic AF, warfarin significantly reduced the risk of systemic thromboembolism including stroke (see Table 4). The risk reduction ranged from 60% to 86% in all except one trial (CAFA: 45%), which was stopped early due to published positive results from two of these trials. The incidence of major bleeding in these trials ranged from 0.6% to 2.7% (see Table 4).

Table 4: Clinical Studies of Warfarin in Non-Rheumatic AF Patients*
 | N |  |  |  | Thromboembolism |  | % Major Bleeding
Study | Warfarin-Treated Patients | Control Patients | PT Ratio | INR | % Risk Reduction | p-value | Warfarin-Treated Patients | Control Patients
AFASAK | 335 | 336 | 1.5 to 2.0 | 2.8 to 4.2 | 60 | 0.027 | 0.6 | 0.0
SPAF | 210 | 211 | 1.3 to 1.8 | 2.0 to 4.5 | 67 | 0.01 | 1.9 | 1.9
BAATAF | 212 | 208 | 1.2 to 1.5 | 1.5 to 2.7 | 86 | <0.05 | 0.9 | 0.5
CAFA | 187 | 191 | 1.3 to 1.6 | 2.0 to 3.0 | 45 | 0.25 | 2.7 | 0.5
SPINAF | 260 | 265 | 1.2 to 1.5 | 1.4 to 2.8 | 79 | 0.001 | 2.3 | 1.5
*All study results of warfarin vs. control are based on intention-to-treat analysis and include ischemic stroke and systemic thromboembolism, excluding hemorrhagic stroke and transient ischemic attacks.

Trials in patients with both AF and mitral stenosis suggest a benefit from anticoagulation with warfarin sodium [see Dosage and Administration (2.2)] .

14.2 Mechanical and Bioprosthetic Heart Valves

In a prospective, randomized, open-label, positive-controlled study in 254 patients with mechanical prosthetic heart valves, the thromboembolic-free interval was found to be significantly greater in patients treated with warfarin alone compared with dipyridamole/aspirin-treated patients (p<0.005) and pentoxifylline/aspirin-treated patients (p<0.05). The results of this study are presented in Table 5.

Table 5: Prospective, Randomized, Open-Label, Positive-Controlled Clinical Study of Warfarin in Patients with Mechanical Prosthetic Heart Valves
 | Patients Treated With
Event | Warfarin | Dipyridamole/Aspirin | Pentoxifylline/Aspirin
Thromboembolism | 2.2/100 py | 8.6/100 py | 7.9/100 py
Major Bleeding | 2.5/100 py | 0.0/100 py | 0.9/100 py
py=patient years

In a prospective, open-label, clinical study comparing moderate (INR 2.65) versus high intensity (INR 9.0) warfarin therapies in 258 patients with mechanical prosthetic heart valves, thromboembolism occurred with similar frequency in the two groups (4.0 and 3.7 events per 100 patient years, respectively). Major bleeding was more common in the high intensity group. The results of this study are presented in Table 6.

Table 6: Prospective, Open-Label Clinical Study of Warfarin in Patients with Mechanical Prosthetic Heart Valves
Event | Moderate Warfarin Therapy INR 2.65 | High Intensity Warfarin Therapy INR 9.0
Thromboembolism | 4.0/100 py | 3.7/100 py
Major Bleeding | 0.95/100 py | 2.1/100 py
py=patient years

In a randomized trial in 210 patients comparing two intensities of warfarin therapy (INR 2.0 to 2.25 vs. INR 2.5 to 4.0) for a three-month period following tissue heart valve replacement, thromboembolism occurred with similar frequency in the two groups (major embolic events 2.0% vs. 1.9%, respectively, and minor embolic events 10.8% vs. 10.2%, respectively). Major hemorrhages occurred in 4.6% of patients in the higher intensity INR group compared to zero in the lower intensity INR group.

14.3 Myocardial Infarction

WARIS (The Warfarin Re-Infarction Study) was a double-blind, randomized study of 1214 patients 2 to 4 weeks post-infarction treated with warfarin to a target INR of 2.8 to 4.8. The primary endpoint was a composite of total mortality and recurrent infarction. A secondary endpoint of cerebrovascular events was assessed. Mean follow-up of the patients was 37 months. The results for each endpoint separately, including an analysis of vascular death, are provided in Table 7.

Table 7: WARIS – Endpoint Analysis of Separate Events
 |  |  |  | % Risk
 | Warfarin | Placebo |  | Reduction
Event | (N=607) | (N=607) | RR (95% CI) | (p-value)
Total Patient Years of
Follow-up | 2018 | 1944
Total Mortality | 94 (4.7/100 py) | 123 (6.3/100 py) | 0.76 (0.60, 0.97) | 24 (p=0.030)
Vascular Death | 82 (4.1/100 py) | 105 (5.4/100 py) | 0.78 (0.60, 1.02) | 22 (p=0.068)
Recurrent MI | 82 (4.1/100 py) | 124 (6.4/100 py) | 0.66 (0.51, 0.85) | 34 (p=0.001)
Cerebrovascular Event | 20 (1.0/100 py) | 44 (2.3/100 py) | 0.46 (0.28, 0.75) | 54 (p=0.002)
RR=Relative risk; Risk reduction=(1 - RR); CI=Confidence interval; MI=Myocardial infarction; py=patient years

WARIS II (The Warfarin, Aspirin, Re-Infarction Study) was an open-label, randomized study of 3630 patients hospitalized for acute myocardial infarction treated with warfarin to a target INR

2.8 to 4.2, aspirin 160 mg per day, or warfarin to a target INR 2.0 to 2.5 plus aspirin 75 mg per day prior to hospital discharge. The primary endpoint was a composite of death, nonfatal reinfarction, or thromboembolic stroke. The mean duration of observation was approximately 4 years. The results for WARIS II are provided in the Table 8.

Table 8: WARIS II – Distribution of Events According to Treatment Group
Event | Aspirin (N=1206) | Warfarin (N=1216) | Aspirin plus Warfarin (N=1208) | Rate Ratio (95% CI) | p-value
 | No. of Events
Major Bleedinga | 8 | 33 | 28 | 3.35b (ND) 4.00c (ND) | ND ND
Minor Bleedingd | 39 | 103 | 133 | 3.21b (ND) 2.55c (ND) | ND ND
Composite Endpointse | 241 | 203 | 181 | 0.81 (0.69 to 0.95)b 0.71 (0.60 to 0.83)c | 0.03 0.001
Reinfarction | 117 | 90 | 69 | 0.56 (0.41 to 0.78)b 0.74 (0.55 to 0.98)c | <0.001 0.03
Thromboembolic Stroke | 32 | 17 | 17 | 0.52 (0.28 to 0.98)b 0.52 (0.28 to 0.97)c | 0.03 0.03
Death | 92 | 96 | 95 |  | 0.82
a Major bleeding episodes were defined as nonfatal cerebral hemorrhage or bleeding necessitating surgical intervention or blood transfusion.
b The rate ratio is for aspirin plus warfarin as compared with aspirin.
c The rate ratio is for warfarin as compared with aspirin.
d Minor bleeding episodes were defined as non-cerebral hemorrhage not necessitating surgical intervention or blood transfusion.
e Includes death, nonfatal reinfarction, and thromboembolic cerebral stroke.
CI=confidence interval
ND=not determined

There were approximately four times as many major bleeding episodes in the two groups receiving warfarin than in the group receiving aspirin alone. Major bleeding episodes were not more frequent among patients receiving aspirin plus warfarin than among those receiving warfarin alone, but the incidence of minor bleeding episodes was higher in the combined therapy group.

15 REFERENCES

OSHA Hazardous Drugs. OSHA.http://www.osha.gov/SLTC/hazardousdrugs/index.html.

HOW SUPPLIED

Warfarin Sodium Tablets USP, 5 mg are supplied as peach to light peach, oval shaped uncoated scored tablets with debossing ‘766’ and ‘5’ on either side of the breakline on one side and ‘AN’ on the other side. They are available as follows:

NDC: 70518-2382-00

NDC: 70518-2382-01

NDC: 70518-2382-02

NDC: 70518-2382-03

NDC: 70518-2382-04

PACKAGING: 100 in 1 BOX

PACKAGING: 1 in 1 POUCH

PACKAGING: 90 in 1 BOTTLE PLASTIC

PACKAGING: 30 in 1 BOTTLE PLASTIC

PACKAGING: 30 in 1 BLISTER PACK

Special Handling

Procedures for proper handling and disposal of potentially hazardous drugs should be considered. Guidelines on this subject have been published [see REFERENCES (15)].

Pharmacy and clinical personnel who are pregnant should avoid exposure to crushed or broken tablets [see USE IN SPECIFIC POPULATIONS (8.1)].

Repackaged and Distributed By:

Remedy Repack, Inc.

625 Kolter Dr. Suite #4 Indiana, PA 1-724-465-8762

17 PATIENT COUNSELING INFORMATION

Advise the patient to read the FDA-approved patient labeling (Medication Guide).

Instructions for Patients

Advise patients to:

- Strictly adhere to the prescribed dosage schedule [see Dosage and Administration (2.1)] .

- If the prescribed dose of warfarin sodium is missed, take the dose as soon as possible on the same day but do not take a double dose of warfarin sodium the next day to make up for missed doses [see Dosage and Administration (2.6)] .
- Obtain prothrombin time tests and make regular visits to their physician or clinic to monitor therapy [see Dosage and Administration (2.1)] .
- Be aware that if therapy with warfarin sodium is discontinued, the anticoagulant effects of warfarin sodium may persist for about 2 to 5 days [see Clinical Pharmacology (12.2)].
- Avoid any activity or sport that may result in traumatic injury [see Use in Specific Populations (8.4)]. And to tell their physician if they fall often as this may increase their risk for complications.
- Eat a normal, balanced diet to maintain a consistent intake of vitamin K. Avoid drastic changes in dietary habits, such as eating large amounts of leafy, green vegetables [see Drug Interactions (7.5)] .
- Contact their physician to report any serious illness, such as severe diarrhea, infection, or fever [see Warnings and Precautions (5)and Adverse Reactions (6)] .
- Immediately contact their physician when experiencing pain and discoloration of the skin (a purple bruise like rash) mostly on areas of the body with a high fat content, such as breasts, thighs, buttocks, hips and abdomen [see Warnings and Precautions (5.2)] .
- Immediately contact their physician when experiencing any unusual symptom or pain since warfarin sodium may cause small cholesterol or athero emboli. On feet it may appear as a sudden cool, painful, purple discoloration of toe(s) or forefoot [see Warnings and Precautions (5.5)] .
- Immediately contact their physician when taking warfarin sodium after any heparin formulation therapy and experiencing bloody or black stools or appearence of bruises, or bleeding [see Warnings and Precautions (5.6)] .
- To tell all of their healthcare professionals and dentists that they are taking warfarin sodium. This should be done before they have any surgery or dental procedure [see Dosage and Administration (2.7)] .
- Carry identification stating that they are taking warfarin sodium.

Bleeding Risks

Advise patients to:

- Notify their physician immediately if any unusual bleeding or symptoms occur. Signs and symptoms of bleeding include: pain, swelling or discomfort, prolonged bleeding from cuts, increased menstrual flow or vaginal bleeding, nosebleeds, bleeding of gums from brushing, unusual bleeding or bruising, red or dark brown urine, red or tar black stools, headache, dizziness, or weakness [see Box Warning and Warnings and Precautions (5.1)] .

Concomitant Medications and Botanicals (Herbals)

Advise patients to:

- Not take or discontinue any other drug, including salicylates (e.g., aspirin and topical analgesics), other over-the-counter drugs, and botanical (herbal) products except on advice of your physician [see Drug Interactions (7)] .

Pregnancy and Nursing

Advise patients to:

- Notify their physician if they are pregnant or planning to become pregnant or considering breast feeding [see Use in Specific Populations (8.1, 8.2, 8.3)] .
- Avoid warfarin sodium during pregnancy except in pregnant women with mechanical heart valves, who are at risk of thromboembolism [see Contraindications (4)] . Use effective measures to avoid pregnancy while taking warfarin sodium. This is very important because their unborn baby could be seriously harmed if they take warfarin sodium while they are pregnant [see Use in Specific Populations (8.1, 8.3)] .

Repackaged By / Distributed By: RemedyRepack Inc.

625 Kolter Drive, Indiana, PA 15701

(724) 465-8762

MEDICATION GUIDE

Warfarin (WAR-far-in) Sodium Tablets, USP (Crystalline)

What is the most important information I should know about warfarin sodium?

Warfarin sodium can cause bleeding which can be serious and sometimes lead to death. This is because warfarin sodium is a blood thinner medicine that lowers the chance of blood clots forming in your body.

- You may have a higher risk of bleeding if you take warfarin sodium and:

- are 65 years of age or older
- have a history of stomach or intestinal bleeding
- have high blood pressure (hypertension)
- have a history of stroke, or “mini-stroke” (transient ischemic attack or TIA)
- have serious heart disease
- have a low blood count or cancer
- have had trauma, such as an accident or surgery
- have kidney problems
- take other medicines that increase your risk of bleeding, including:

- a medicine that contains heparin
- other medicines to prevent or treat blood clots
- nonsteroidal anti-inflammatory drugs (NSAIDs)

- take warfarin sodium for a long time. Warfarin sodium is the active ingredient in warfarin sodium tablets.

Tell your healthcare provider if you take any of these medicines. Ask your healthcare provider if you are not sure if your medicine is one listed above.

Many other medicines can interact with warfarin sodium and affect the dose you need or increase warfarin sodium side effects. Do not change or stop any of your medicines or start any new medicines before you talk to your healthcare provider.

Do not take other medicines that contain warfarin sodium while taking warfarin sodium tablets.

- Get your regular blood test to check for your response to warfarin sodium. This blood test is called an INR test. The INR test checks to see how fast your blood clots. Your healthcare provider will decide what INR numbers are best for you. Your dose of warfarin sodium will be adjusted to keep your INR in a target range for you.
- Call your healthcare provider right away if you get any of the following signs or symptoms of bleeding problems:

- pain, swelling, or discomfort
- headaches, dizziness, or weakness
- unusual bruising (bruises that develop without known cause or grow in size)
- nosebleeds
- bleeding gums
- bleeding from cuts takes a long time to stop
- menstrual bleeding or vaginal bleeding that is heavier than normal
- pink or brown urine
- red or black stools
- coughing up blood
- vomiting blood or material that looks like coffee grounds

- Some foods and beverages can interact with warfarin sodium and affect your treatment and dose.

- Eat a normal, balanced diet. Talk to your healthcare provider before you make any diet changes. Do not eat large amounts of leafy, green vegetables. Leafy, green vegetables contain vitamin K. Certain vegetable oils also contain large amounts of vitamin K. Too much vitamin K can lower the effect of warfarin sodium.

- Always tell all of your healthcare providers that you take warfarin sodium.
- Wear or carry information that you take warfarin sodium.

See “What are the possible side effects of warfarin sodium?” for more information about side effects.

What is warfarin sodium?

Warfarin sodium is prescription medicine used to treat blood clots and to lower the chance of blood clots forming in your body. Blood clots can cause a stroke, heart attack, or other serious conditions if they form in the legs or lungs.

Who should not take warfarin sodium?

Do not take warfarin sodium if:

- your risk of having bleeding problems is higher than the possible benefit of treatment. Your healthcare provider will decide if warfarin sodium is right for you.
- you are pregnant unless you have a mechanical heart valve. Warfarin sodium may cause birth defects, miscarriage, or death of your unborn baby.
- you are allergic to warfarin or any of the other ingredients in warfarin sodium tablets. See the end of this leaflet for a complete list of ingredients in warfarin sodium tablets.

Before taking warfarin sodium, tell your healthcare provider about all of your medical conditions, including if you:

- have bleeding problems
- fall often
- have liver problems
- have kidney problems or are undergoing dialysis
- have high blood pressure
- have a heart problem called congestive heart failure
- have diabetes
- plan to have any surgery or a dental procedure
- are pregnant or plan to become pregnant. See “ Who should not take warfarin sodium?”

- Your healthcare provider will do a pregnancy test before you start treatment with warfarin sodium. Females who can become pregnant should use effective birth control during treatment, and for at least 1 month after the last dose of warfarin sodium.

- are breastfeeding. You and your healthcare provider should decide if you will take warfarin sodium and breastfeed. Check your baby for bruising or bleeding if you take warfarin sodium and breastfeed.

Tell all of your healthcare providers and dentists that you are taking warfarin sodium. They should talk to the healthcare provider who prescribed warfarin sodium for you before you have any surgery or dental procedure. Your warfarin sodium may need to be stopped for a short time or you may need your dose adjusted.

Tell your healthcare provider about all the medicines you take, including prescription and over-the-counter medicines, vitamins, and herbal supplements. Some of your other medicines may affect the way warfarin sodium works. Certain medicines may increase your risk of bleeding. See “ What is the most important information I should know about warfarin sodium?”

How should I take warfarin sodium?

- Take warfarin sodium exactly as prescribed. Your healthcare provider will adjust your dose from time to time depending on your response to warfarin sodium.
- You must have regular blood tests and visits with your healthcare provider to monitor your condition.
- If you miss a dose of warfarin sodium, call your healthcare provider. Take the dose as soon as possible on the same day. Do not take a double dose of warfarin sodium the next day to make up for a missed dose.
- Call your healthcare provider right away if you:
- take too much warfarin sodium
- are sick with diarrhea, an infection, or have a fever
- fall or injure yourself, especially if you hit your head. Your healthcare provider may need to check you.

What should I avoid while taking warfarin sodium?

- Do not do any activity or sport that may cause a serious injury.
  What are the possible side effects of warfarin sodium?
  Warfarin sodium may cause serious side effects, including:
- See “ What is the most important information I should know about warfarin sodium?”
- Death of skin tissue (skin necrosis or gangrene). This can happen soon after starting warfarin sodium. It happens because blood clots form and block blood flow to an area of your body. Call your healthcare provider right away if you have pain, color, or temperature change to any area of your body. You may need medical care right away to prevent death or loss (amputation) of your affected body part.
- Kidney problems. Kidney injury may happen in people who take warfarin sodium. Tell your healthcare provider right away if you develop blood in your urine. Your healthcare provider may do tests more often during treatment with warfarin sodium to check for bleeding if you already have kidney problems.
- “Purple toes syndrome.” Call your healthcare provider right away if you have pain in your toes and they look purple in color or dark in color.

These are not all of the side effects of warfarin sodium. For more information, ask your healthcare provider or pharmacist.

Call your doctor for medical advice about side effects. You may report side effects to FDA at 1-800-FDA-1088.

How should I store warfarin sodium tablets?

- Store warfarin sodium tablets at 20° to 25°C (68° to 77°F); excursions permitted between 15° to 30°C (59° to 86°F).
- Keep warfarin sodium tablets in a tightly closed container.
- Keep warfarin sodium tablets out of the light and moisture.
- Follow your healthcare provider or pharmacist instructions about the right way to throw away outdated or unused warfarin sodium.
- Females who are pregnant should not handle crushed or broken warfarin sodium tablets.

Keep warfarin sodium tablets and all medicines out of the reach of children.
General information about the safe and effective use of warfarin sodium.
Medicines are sometimes prescribed for purposes other than those listed in a Medication Guide. Do not use warfarin sodium for a condition for which it was not prescribed. Do not give warfarin sodium to other people, even if they have the same symptoms that you have. It may harm them.
You can ask your healthcare provider or pharmacist for information about warfarin sodium that is written for health professionals.

If you would like more information, go to www.amneal.com or call 1-877-835-5472.

What are the ingredients in warfarin sodium tablets?

Active ingredient: Warfarin Sodium

Inactive ingredients: Hydroxypropyl Cellulose, Lactose Monohydrate, Magnesium Stearate and Pregelatinized Starch. The following tablets contain:

1 mg: D&C Red No. 6 Barium Lake
2 mg: FD&C Blue No. 2 Aluminum Lake and FD&C Red No. 40 Aluminum Lake
2-1/2 mg: D&C Yellow No. 10 Aluminum Lake and FD&C Blue No. 1 Aluminum Lake
3 mg: FD&C Yellow No. 6 Aluminum Lake, FD&C Blue No. 2 Aluminum Lake, and FD&C Red No. 40 Aluminum Lake
4 mg: FD&C Blue No. 1 Aluminum Lake
5 mg: FD&C Yellow No. 6 Aluminum Lake
6 mg: FD&C Yellow No. 6 Aluminum Lake and FD&C Blue No. 1 Aluminum Lake
7-1/2 mg: D&C Yellow No. 10 Aluminum Lake and FD&C Yellow No. 6 Aluminum Lake

This Medication Guide has been approved by the U.S. Food and Drug Administration.

Repackaged By / Distributed By: RemedyRepack Inc.

625 Kolter Drive, Indiana, PA 15701

(724) 465-8762

PACKAGE LABEL

DRUG: Warfarin Sodium

GENERIC: Warfarin

DOSAGE: TABLET

ADMINSTRATION: ORAL

NDC: 70518-2382-0

NDC: 70518-2382-1

NDC: 70518-2382-2

NDC: 70518-2382-3

NDC: 70518-2382-4

COLOR: orange

SHAPE: OVAL

SCORE: Two even pieces

SIZE: 11 mm

IMPRINT: 766;5;AN

PACKAGING: 1 in 1 POUCH

OUTER PACKAGING: 100 in 1 BOX

PACKAGING: 90 in 1 BOTTLE PLASTIC

PACKAGING: 30 in 1 BOTTLE PLASTIC

PACKAGING: 30 in 1 BLISTER PACK

ACTIVE INGREDIENT(S):

- WARFARIN SODIUM 5mg in 1

INACTIVE INGREDIENT(S):

- HYDROXYPROPYL CELLULOSE (70000 WAMW)
- LACTOSE MONOHYDRATE
- MAGNESIUM STEARATE
- STARCH, CORN
- FD&C YELLOW NO. 6